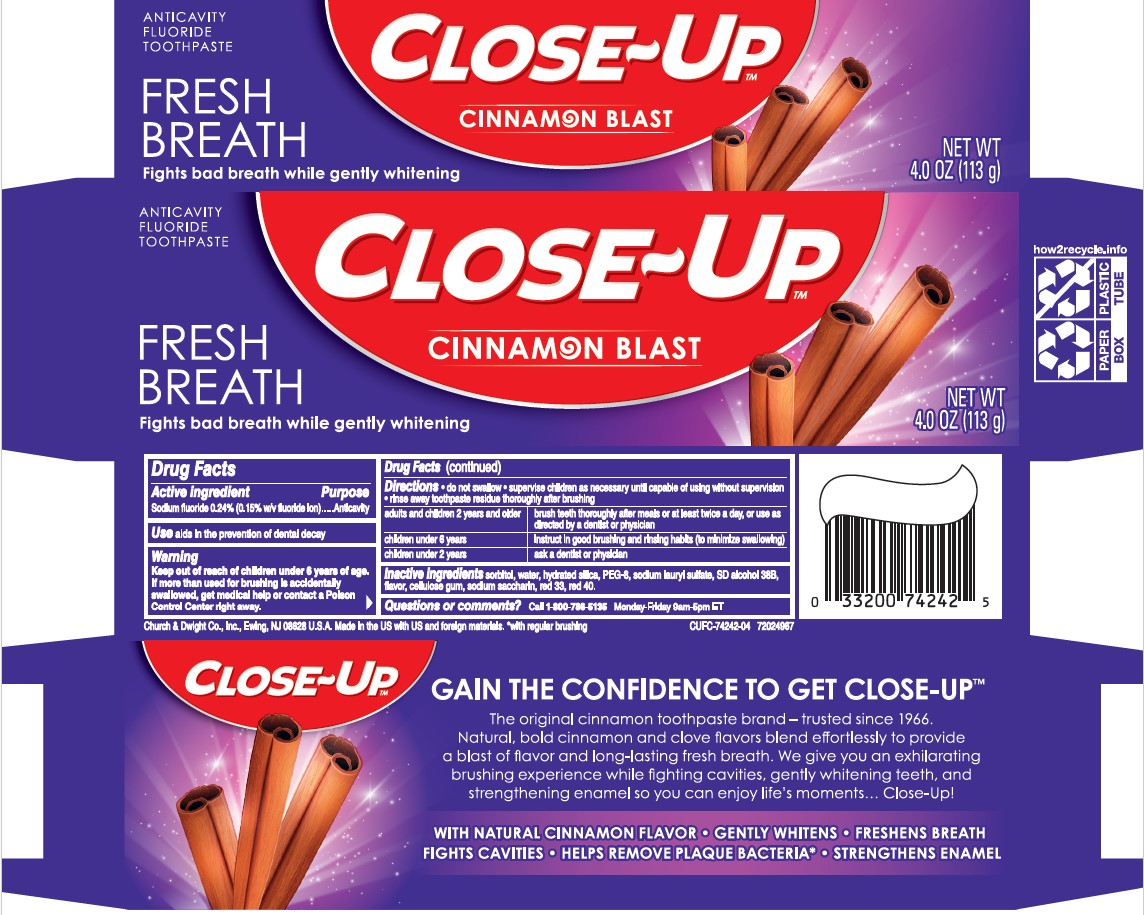 DRUG LABEL: CLOSE UP
NDC: 10237-644 | Form: GEL, DENTIFRICE
Manufacturer: Church & Dwight Co., Inc.
Category: otc | Type: HUMAN OTC DRUG LABEL
Date: 20250909

ACTIVE INGREDIENTS: SODIUM FLUORIDE 2.4 mg/1 g
INACTIVE INGREDIENTS: WATER; HYDRATED SILICA; PEG-8 STEARATE; SORBITOL; SODIUM LAURYL SULFATE; ALCOHOL; CARBOXYMETHYLCELLULOSE SODIUM, UNSPECIFIED; D&C RED NO. 33; FD&C RED NO. 40; SACCHARIN SODIUM

CLOSE UP Freshening Gel

Active ingredients
Sodium fluoride (0.24%)

Purpose
Anticavity toothpaste

INDICATIONS AND USAGE

Use:Aids in the prevention of dental decay

Warnings
Keep out of reach of children under 6 years of age .

WARNINGS

If more than used for brushing is accidentally swallowed, get medical help or contact a Poison Control Center right away.

DOSAGE AND ADMINISTRATION

Directions do not swallow supervise children as necessary until capable of using without supervision

adults and children 2 years and older brush teeth thoroughly after meals or at least twice a day, or use as directed by a dentist or physician
children under 6 years instruct in good brushing and rinsing habits (to minimize swallowing)
children under 2 years ask a dentist or physician

INACTIVE INGREDIENT

Inactive ingredients sorbitol, water, hydrated silica, PEG-8, sodium lauryl sulfate, SD alcohol 38-B, flavor, cellulose gum, sodium saccharin, red 33, red 40.

Questions or comments? Call 1-800-786-5135Monday-Friday 9am-5pm ET

Principal Display Panel

ANITCAVITY FLOURIDE TOOTHPASTE

FRESH BREATH

Fights bad breath while gently whitening

CLOSE-UP

CINNAMON BLAST

NET WT. 4.0 OZ. (113g)